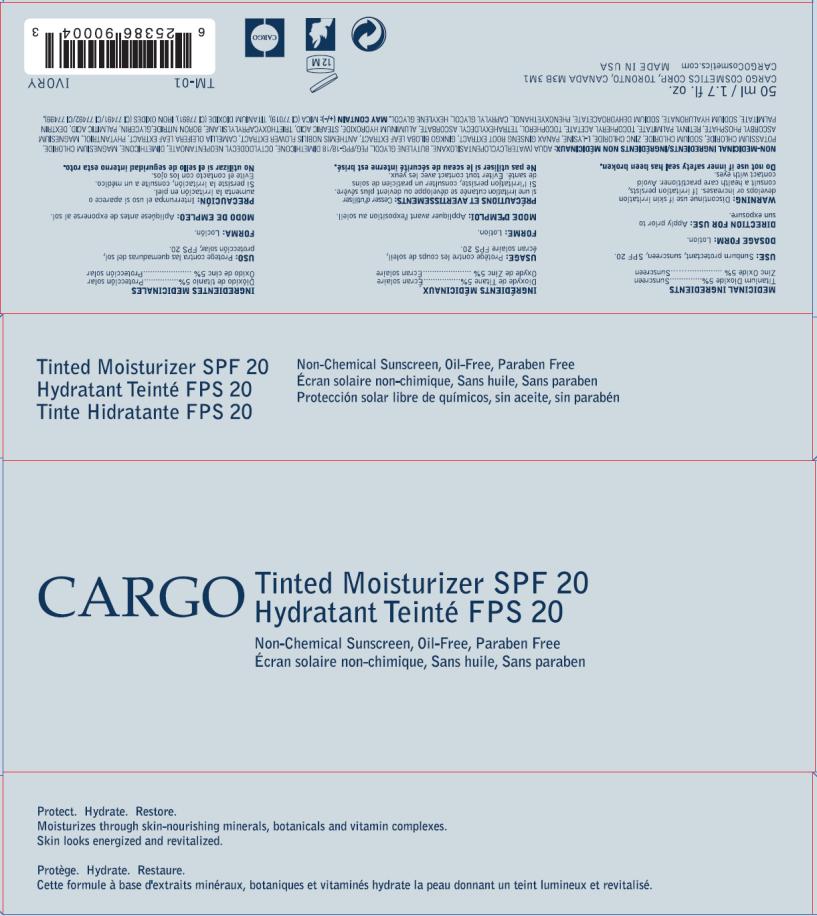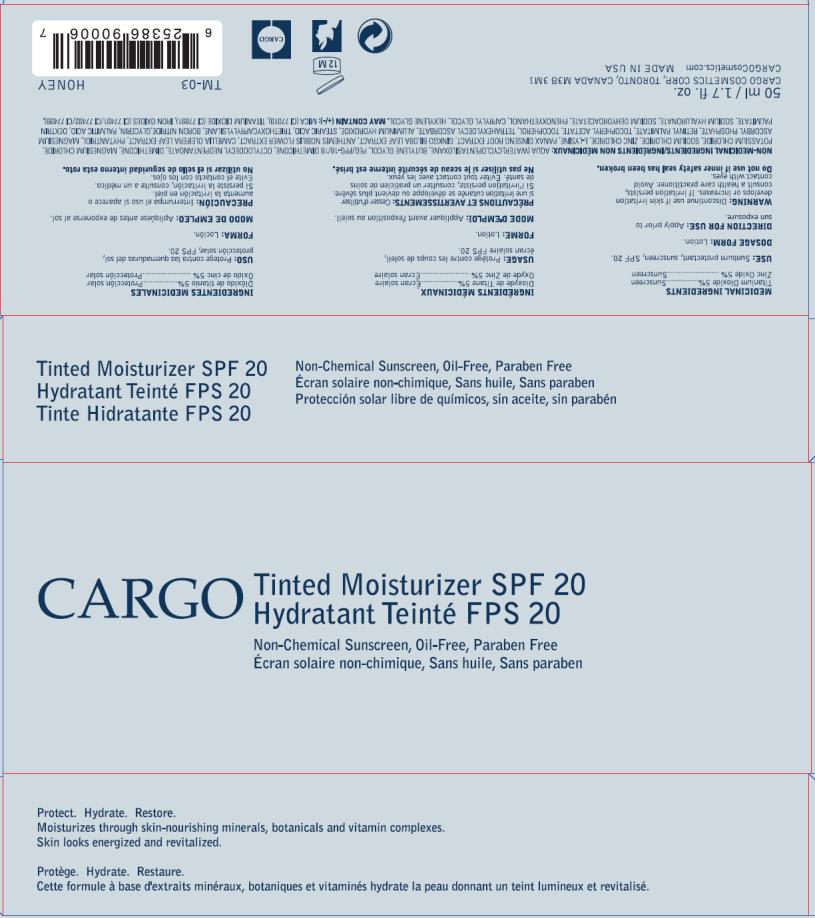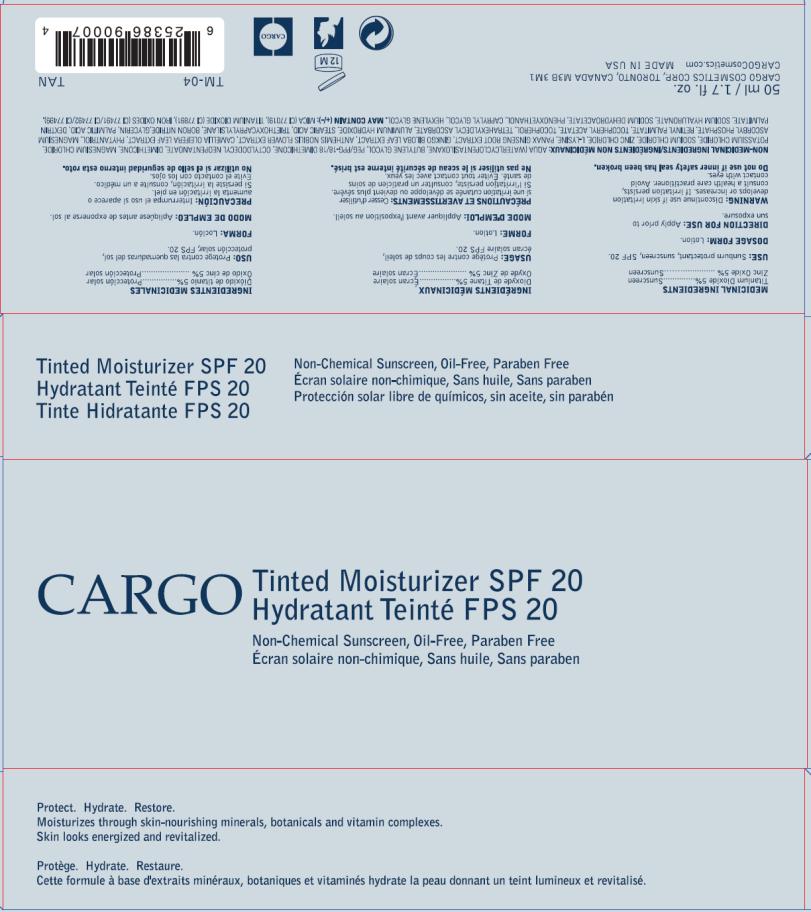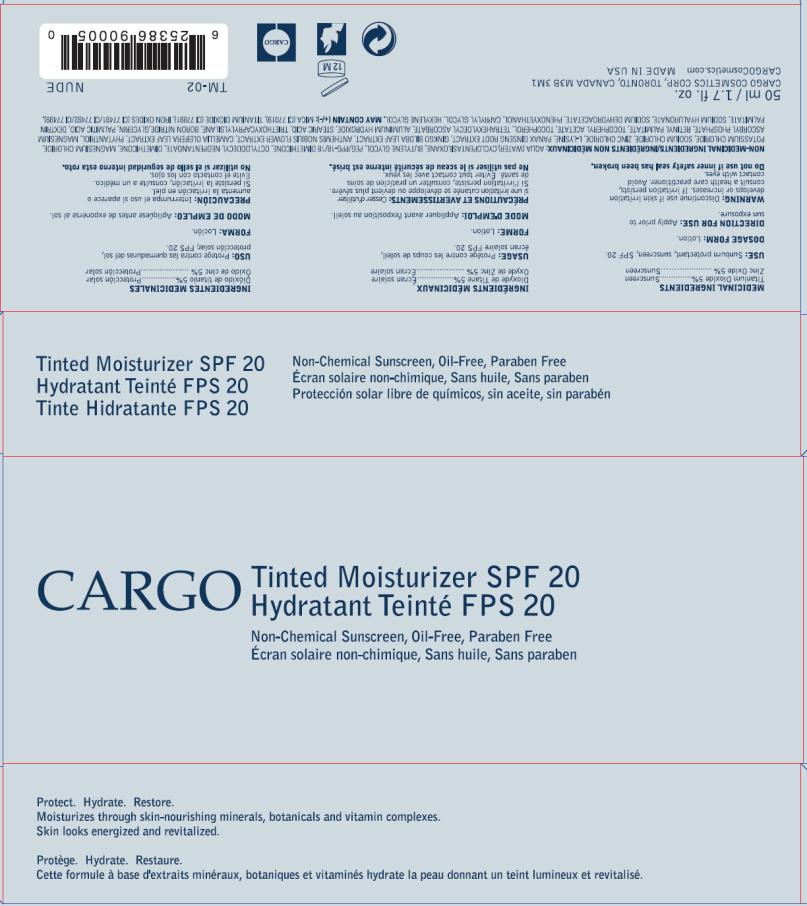 DRUG LABEL: Cargo Tinted Moisturizer SPF 20
NDC: 76053-001 | Form: LOTION
Manufacturer: Cargo Cosmetics Corp.
Category: otc | Type: HUMAN OTC DRUG LABEL
Date: 20110415

ACTIVE INGREDIENTS: TITANIUM DIOXIDE 2.5 mL/1 mL; ZINC OXIDE 2.5 mL/1 mL
INACTIVE INGREDIENTS: WATER; CYCLOMETHICONE 5; BUTYLENE GLYCOL; DIMETHICONE; MAGNESIUM CHLORIDE; POTASSIUM CHLORIDE; SODIUM CHLORIDE; ZINC CHLORIDE; ASIAN GINSENG; CHAMAEMELUM NOBILE FLOWER; CAMELLIA OLEIFERA LEAF; PHYTANTRIOL; MAGNESIUM ASCORBYL PHOSPHATE; .ALPHA.-TOCOPHEROL ACETATE, D-; ALPHA-TOCOPHEROL; TETRAHEXYLDECYL ASCORBATE; ALUMINUM HYDROXIDE; STEARIC ACID; TRIETHOXYCAPRYLYLSILANE; BORON NITRIDE; GLYCERIN; PALMITIC ACID; SODIUM DEHYDROACETATE; PHENOXYETHANOL; CAPRYLYL GLYCOL; HEXYLENE GLYCOL

Cargo Tinted Moisturizer SPF 20

Cargo Tinted Moisturizer SPF 20 - Ivory

MEDICINAL INGREDIENTS

Titanium Dioxide 5%

Zinc Oxide 5%

PURPOSE

Sunscreen

USE

Sunburn protectant, sunscreen, SPF 20

DOSAGE FORM

Lotion

DIRECTION FOR USE

Apply prior to sun exposure

WARNING

Discontinue use if skin irritation develops or increases. If irritation persists, consult a health care practitioner. Avoid contact with eyes.

Do not use

if inner safety seal has been broken.

NON-MEDICINAL INGREDIENTS/INGRÉDIENTS NON MÉDICINAUX:

AQUA (WATER), CYCLOPENTASILOXANE, BUTYLENE GLYCOL, PEG/PPG-18/18 DIMETHICONE, OCTYLDODECYL, NEOPENTANOATE, DIMETHICONE, MAGNESIUM CHLORIDE, POTASSIUM CHLORIDE, SODIUM CHLORIDE, ZINC CHLORIDE, L-LYSINE, PANAX GINSENG ROOT EXTRACT, GINKGO BILOBA LEAF EXTRACT, ANTHEMIS NOBILIS FLOWER EXTRACT, CAMELLIA OLEIFERA LEAF EXTRACT, PHYTANTRIOL, MAGNESIUM ASCORBYL PHOSPHATE, RETINYL PALMITATE, TOCOPHERYL ACETATE, TOCOPHEROL, TETRAHEXYLDECYL ASCORBATE, ALUMINUM HYDROXIDE, STEARIC ACID, TRIETHOXYCAPRYLYLSILANE, BORON NITRIDE, GLYCERIN, PALMITIC ACID, DEXTRIN PALMITATE, SODIUM HYALURONATE, SODIUM DEHYDROACETATE, PHENOXYETHANOL, CAPRYLYL GLYCOL, HEXYLENE GLYCOL.

MAY CONTAIN (+/-): MICA (CI 77019), TITANIUM DIOXIDE (CI 77891), IRON OXIDES (CI 77491/ CI 77492/ CI 77499).

Cargo Tinted Moisturizer SPF 20 - Honey

MEDICINAL INGREDIENTS

Titanium Dioxide 5%

Zinc Oxide 5%

PURPOSE

Sunscreen

USE

Sunburn protectant, sunscreen, SPF 20

DOSAGE FORM

Lotion

DIRECTION FOR USE

Apply prior to sun exposure

WARNING

Discontinue use if skin irritation develops or increases. If irritation persists, consult a health care practitioner. Avoid contact with eyes.

Do not use

if inner safety seal has been broken.

NON-MEDICINAL INGREDIENTS/INGRÉDIENTS NON MÉDICINAUX:

AQUA (WATER), CYCLOPENTASILOXANE, BUTYLENE GLYCOL, PEG/PPG-18/18 DIMETHICONE, OCTYLDODECYL, NEOPENTANOATE, DIMETHICONE, MAGNESIUM CHLORIDE, POTASSIUM CHLORIDE, SODIUM CHLORIDE, ZINC CHLORIDE, L-LYSINE, PANAX GINSENG ROOT EXTRACT, GINKGO BILOBA LEAF EXTRACT, ANTHEMIS NOBILIS FLOWER EXTRACT, CAMELLIA OLEIFERA LEAF EXTRACT, PHYTANTRIOL, MAGNESIUM ASCORBYL PHOSPHATE, RETINYL PALMITATE, TOCOPHERYL ACETATE, TOCOPHEROL, TETRAHEXYLDECYL ASCORBATE, ALUMINUM HYDROXIDE, STEARIC ACID, TRIETHOXYCAPRYLYLSILANE, BORON NITRIDE, GLYCERIN, PALMITIC ACID, DEXTRIN PALMITATE, SODIUM HYALURONATE, SODIUM DEHYDROACETATE, PHENOXYETHANOL, CAPRYLYL GLYCOL, HEXYLENE GLYCOL.

MAY CONTAIN (+/-): MICA (CI 77019), TITANIUM DIOXIDE (CI 77891), IRON OXIDES (CI 77491/ CI 77492/ CI 77499).

Cargo Tinted Moisturizer SPF 20 - Tan

MEDICINAL INGREDIENTS

Titanium Dioxide 5%

Zinc Oxide 5%

PURPOSE

Sunscreen

USE

Sunburn protectant, sunscreen, SPF 20

DOSAGE FORM

Lotion

DIRECTION FOR USE

Apply prior to sun exposure

WARNING

Discontinue use if skin irritation develops or increases. If irritation persists, consult a health care practitioner. Avoid contact with eyes.

Do not use

if inner safety seal has been broken.

NON-MEDICINAL INGREDIENTS/INGRÉDIENTS NON MÉDICINAUX:

AQUA (WATER), CYCLOPENTASILOXANE, BUTYLENE GLYCOL, PEG/PPG-18/18 DIMETHICONE, OCTYLDODECYL, NEOPENTANOATE, DIMETHICONE, MAGNESIUM CHLORIDE, POTASSIUM CHLORIDE, SODIUM CHLORIDE, ZINC CHLORIDE, L-LYSINE, PANAX GINSENG ROOT EXTRACT, GINKGO BILOBA LEAF EXTRACT, ANTHEMIS NOBILIS FLOWER EXTRACT, CAMELLIA OLEIFERA LEAF EXTRACT, PHYTANTRIOL, MAGNESIUM ASCORBYL PHOSPHATE, RETINYL PALMITATE, TOCOPHERYL ACETATE, TOCOPHEROL, TETRAHEXYLDECYL ASCORBATE, ALUMINUM HYDROXIDE, STEARIC ACID, TRIETHOXYCAPRYLYLSILANE, BORON NITRIDE, GLYCERIN, PALMITIC ACID, DEXTRIN PALMITATE, SODIUM HYALURONATE, SODIUM DEHYDROACETATE, PHENOXYETHANOL, CAPRYLYL GLYCOL, HEXYLENE GLYCOL.

MAY CONTAIN (+/-): MICA (CI 77019), TITANIUM DIOXIDE (CI 77891), IRON OXIDES (CI 77491/ CI 77492/ CI 77499).

Cargo Tinted Moisturizer SPF 20 - Nude

MEDICINAL INGREDIENTS

Titanium Dioxide 5%

Zinc Oxide 5%

PURPOSE

Sunscreen

USE

Sunburn protectant, sunscreen, SPF 20

DOSAGE FORM

Lotion

DIRECTION FOR USE

Apply prior to sun exposure

WARNING

Discontinue use if skin irritation develops or increases. If irritation persists, consult a health care practitioner. Avoid contact with eyes.

Do not use

if inner safety seal has been broken.

NON-MEDICINAL INGREDIENTS/INGRÉDIENTS NON MÉDICINAUX:

AQUA (WATER), CYCLOPENTASILOXANE, BUTYLENE GLYCOL, PEG/PPG-18/18 DIMETHICONE, OCTYLDODECYL, NEOPENTANOATE, DIMETHICONE, MAGNESIUM CHLORIDE, POTASSIUM CHLORIDE, SODIUM CHLORIDE, ZINC CHLORIDE, L-LYSINE, PANAX GINSENG ROOT EXTRACT, GINKGO BILOBA LEAF EXTRACT, ANTHEMIS NOBILIS FLOWER EXTRACT, CAMELLIA OLEIFERA LEAF EXTRACT, PHYTANTRIOL, MAGNESIUM ASCORBYL PHOSPHATE, RETINYL PALMITATE, TOCOPHERYL ACETATE, TOCOPHEROL, TETRAHEXYLDECYL ASCORBATE, ALUMINUM HYDROXIDE, STEARIC ACID, TRIETHOXYCAPRYLYLSILANE, BORON NITRIDE, GLYCERIN, PALMITIC ACID, DEXTRIN PALMITATE, SODIUM HYALURONATE, SODIUM DEHYDROACETATE, PHENOXYETHANOL, CAPRYLYL GLYCOL, HEXYLENE GLYCOL.

MAY CONTAIN (+/-): MICA (CI 77019), TITANIUM DIOXIDE (CI 77891), IRON OXIDES (CI 77491/ CI 77492/ CI 77499).

PRINCIPAL DISPLAY PANEL

CARGO Tinted Moisturizer SPF 20
Non-Chemical Sunscreen, Oil-Free, Paraben Free
5 ml/ 1.7 fl. oz. IVORY

PRINCIPAL DISPLAY PANEL

CARGO Tinted Moisturizer SPF 20
Non-Chemical Sunscreen, Oil-Free, Paraben Free
5 ml/ 1.7 fl. oz. HONEY

PRINCIPAL DISPLAY PANEL

CARGO Tinted Moisturizer SPF 20
Non-Chemical Sunscreen, Oil-Free, Paraben Free
5 ml/ 1.7 fl. oz. TAN

PRINCIPAL DISPLAY PANEL

CARGO Tinted Moisturizer SPF 20
Non-Chemical Sunscreen, Oil-Free, Paraben Free
5 ml/ 1.7 fl. oz. NUDE